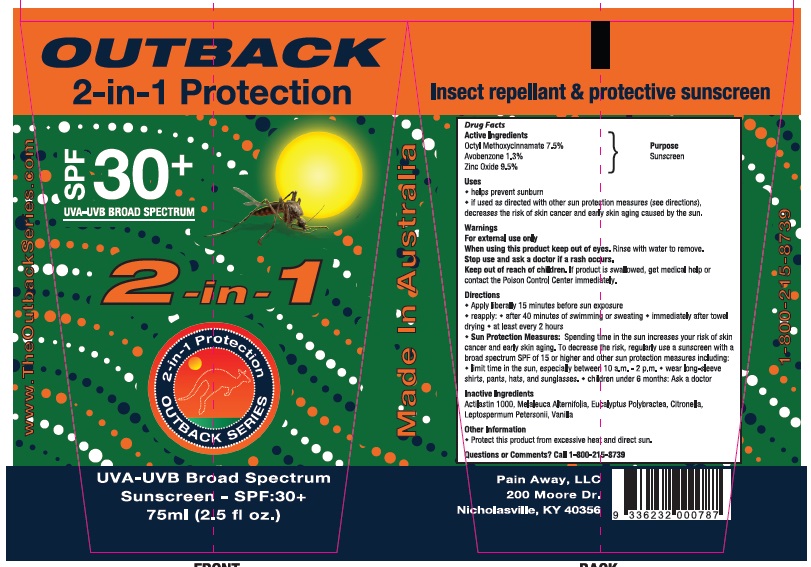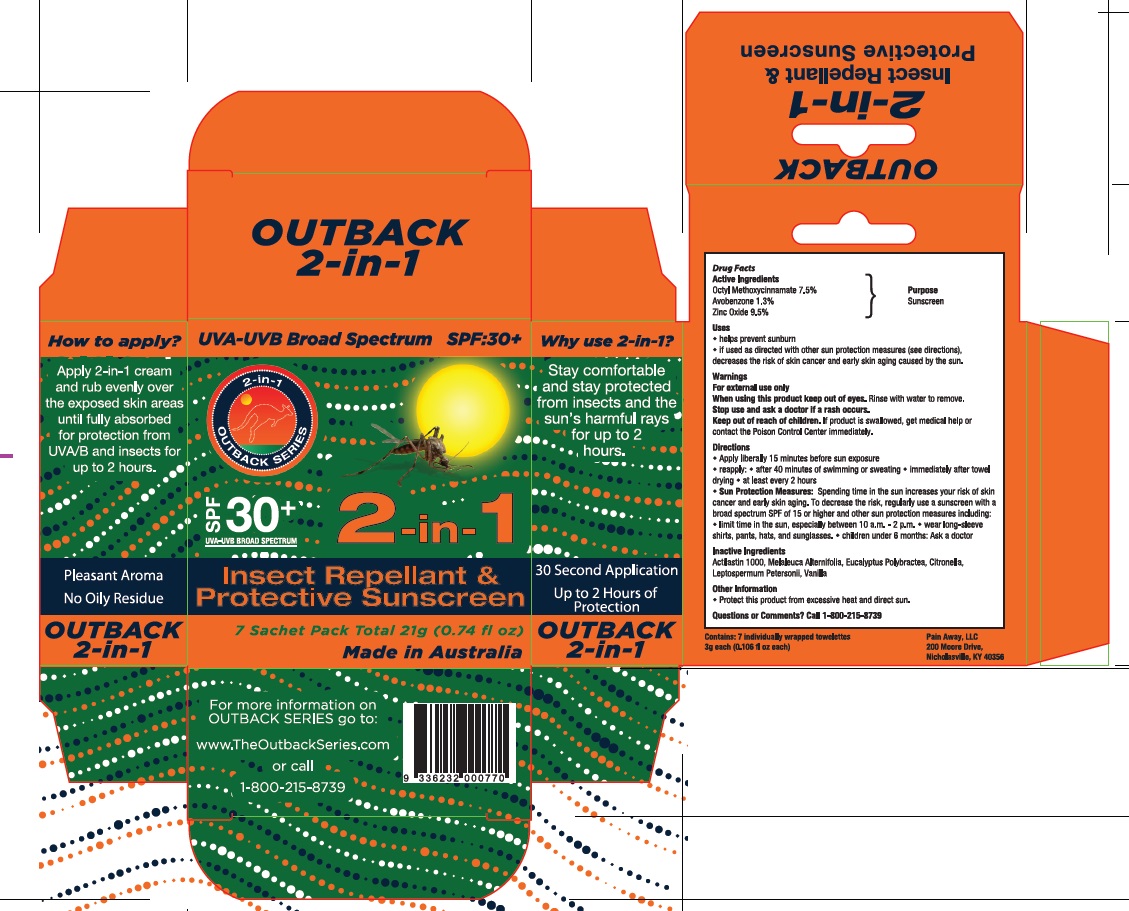 DRUG LABEL: Outback Series 2-in-1 Sunscreen
NDC: 43979-446 | Form: CREAM
Manufacturer: Elmore Oil Company Pty Ltd
Category: otc | Type: HUMAN OTC DRUG LABEL
Date: 20130611

ACTIVE INGREDIENTS: OCTINOXATE 75 mg/1 mL; AVOBENZONE 13 mg/1 mL; Zinc Oxide 80 mg/1 mL
INACTIVE INGREDIENTS: EUCALYPTUS POLYBRACTEA LEAF OIL; LEPTOSPERMUM PETERSONII LEAF OIL; CITRONELLA OIL; TEA TREE OIL

Active ingrdient

Octyl Methoxycinnamate - 7.5%

Avobenzone - 1.3%

Zinc Oxide - 9.5%

Purpose

Sunscreen 30+

Indication and Usage

Helps prevent sunburn. if used as directed with other sun protection measures (see directions), decreases the risk of skin cancer and early skin aging caused by the sun.

Dosage and Administration

Apply liberally 15 minutes before sun exposure reapply: after 40 minutes of swimming or sweating immediately after towel drying at least every 2 hours.

Warnings

For external use only. When using this product keep out of eyes. Rinse with water to remove. Stop use and ask a doctor if a rash occurs. Keep out of reach of children. If product is swallowed, get medical help or contact the Poison Control Center right away.

Sun Protection Measures. Spending time in the sun increases your risk of skin cancer and early skin aging. To decrease the risk, regularly use a sunscreen with a broad spectrum SPF or 15 or higher and other sun protection measures including: limit time in the sun, especially between 10 a.m – 2 p.m. wear long-sleeve shirts, pants, hats and sunglasses. children under 6 months: Ask a doctor.

Inactive Ingredients

Actilastin 1000, Melaleuca Alternifolia, Eucalyptus Polybractea, Citronella, Leptospermum Petersonii, Vanilla

Keep out of Reach of Children